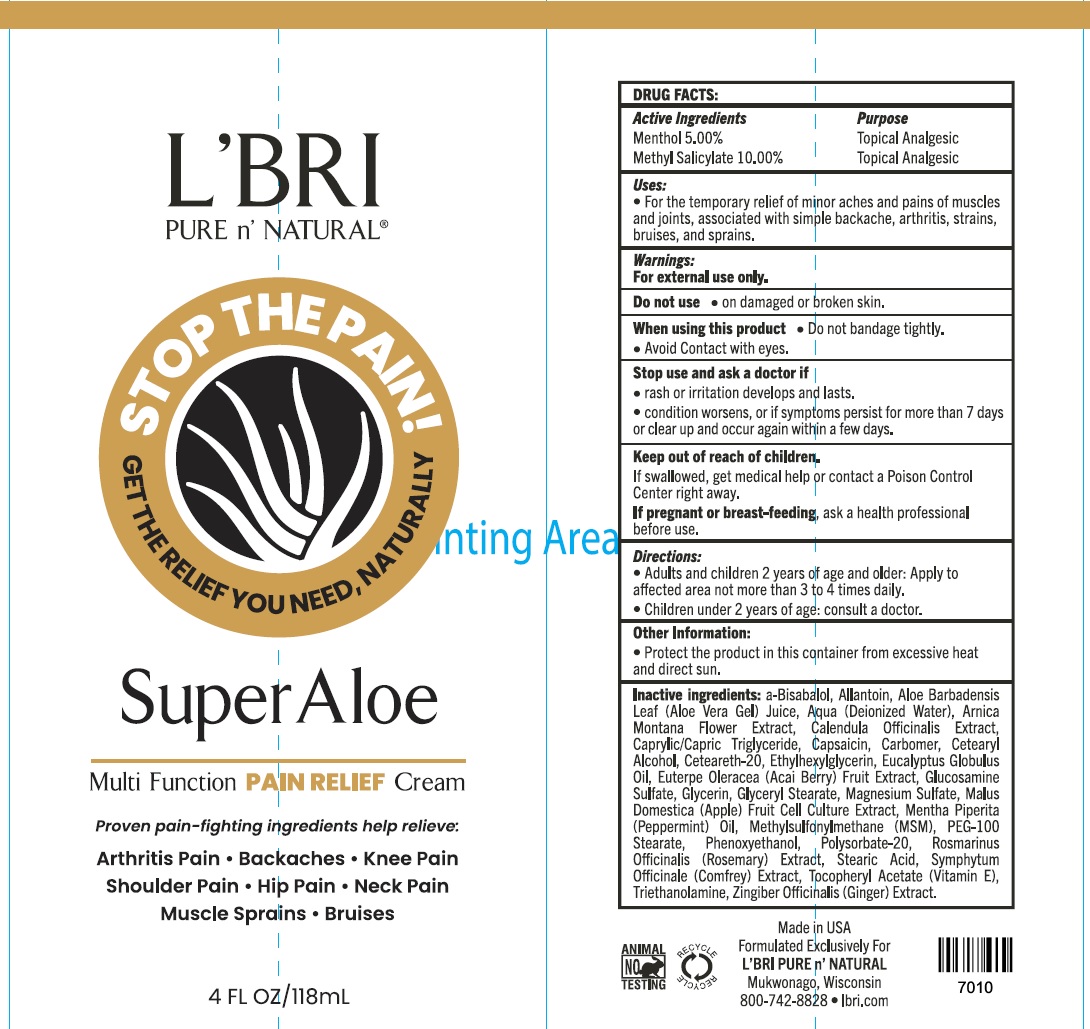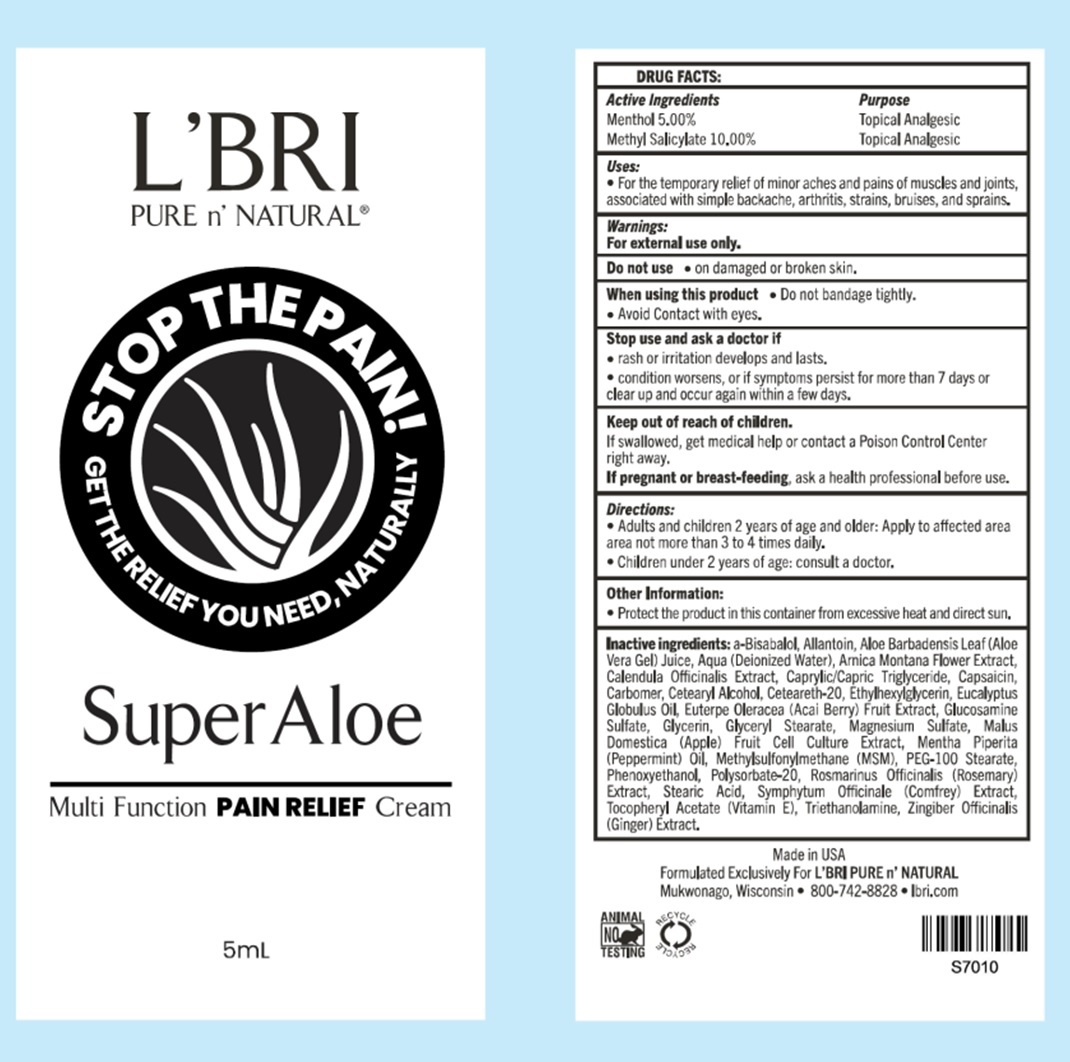 DRUG LABEL: LBRI STOP THE PAIN Super Aloe Pain Relief Cream
NDC: 71238-492 | Form: CREAM
Manufacturer: L'BRI HEALTH AND BEAUTY INC
Category: otc | Type: HUMAN OTC DRUG LABEL
Date: 20250128

ACTIVE INGREDIENTS: MENTHOL 50 mg/1 mL; METHYL SALICYLATE 100 mg/1 mL
INACTIVE INGREDIENTS: MAGNESIUM SULFATE, UNSPECIFIED FORM; APPLE; PEPPERMINT OIL; DIMETHYL SULFONE; PEG-100 STEARATE; PHENOXYETHANOL; POLYSORBATE 20; ROSEMARY; STEARIC ACID; SYMPHYTUM X UPLANDICUM LEAF; .ALPHA.-TOCOPHEROL ACETATE; TROLAMINE; GINGER; ALLANTOIN; ALOE VERA LEAF; WATER; ARNICA MONTANA FLOWER; CALENDULA OFFICINALIS FLOWER; MEDIUM-CHAIN TRIGLYCERIDES; CAPSAICIN; CARBOMER HOMOPOLYMER, UNSPECIFIED TYPE; CETOSTEARYL ALCOHOL; POLYOXYL 20 CETOSTEARYL ETHER; ETHYLHEXYLGLYCERIN; EUCALYPTUS OIL; ACAI; GLUCOSAMINE SULFATE; GLYCERIN; GLYCERYL MONOSTEARATE

L'BRI STOP THE PAIN Super Aloe Pain Relief Cream

Active Ingredients

Menthol 5.00%

Methyl Salicylate 10.00%

Purpose

Topical Analgesic

Uses:

For the temporary relief of minor aches and pains of muscles and joints, associated with simple backache, arthritis, strains, bruises, and sprains.

Warnings:

For external use only.

Do not use

- on damaged or broken skin.

When using this product

- Do not bandage tightly.
- Avoid Contact with eyes.

Stop use and ask a doctor if

rash or irritation develops and lasts. condition worsens, or if symptoms persist for more than 7 days or clear up and occur again within a few days.

Keep out of reach of children.

If swallowed, get medical help or contact a Poison Control Center right away.

If pregnant or breast-feeding,

ask a health professional before use.

Directions:

- Adults and children 2 years of age and older: Apply to affected area not more than 3 to 4 times daily.
- Children under 2 years of age: consult a doctor.

Other Information:

- Protect the product in this container from excessive heat and direct sun.

Inactive ingredients:

a-Bisabolol, Allantoin, Aloe Barbadensis Leaf (Aloe Vera Gel) Juice, Aqua (Deionized Water), Arnica Montana Flower Extract, Calendula Officinalis Extract, Caprylic/Capric Triglyceride, Capsaicin, Carbomer, Cetearyl Alcohol, Ceteareth-20, Ethylhexylglycerin, Eucalyptus Globulus Oil, Euterpe Oleracea (Acai Berry) Fruit Extract, Glucosamine sulfate, Glycerin, Glyceryl Stearate, Magnesium Sulfate, Malus Domestica (Apple) Fruit Cell Culture Extract, Mentha Piperita (Peppermint) Oil, Methylsulfonylmethane (MSM), PEG-100 Stearate, Phenoxyethanol, Polysorbate-20, Rosmarinus Officinalis (Rosemary) Extract, Stearic Acid, Symphytum Offiinale (Comfrey) Extract, Tocopheryl Acetate (Vitamin E), Triethanolamine, ZIngiber Officinalis (Ginger) Extract.